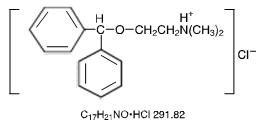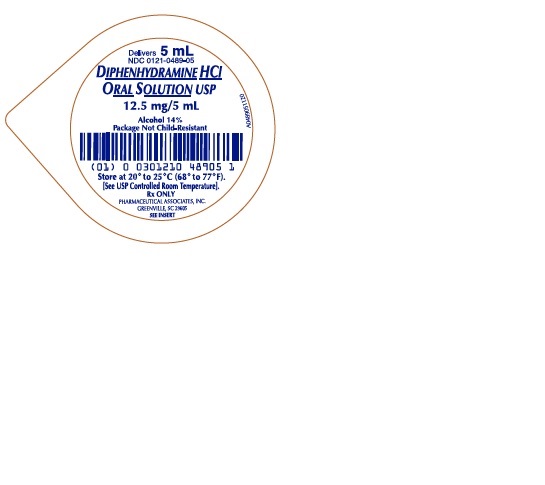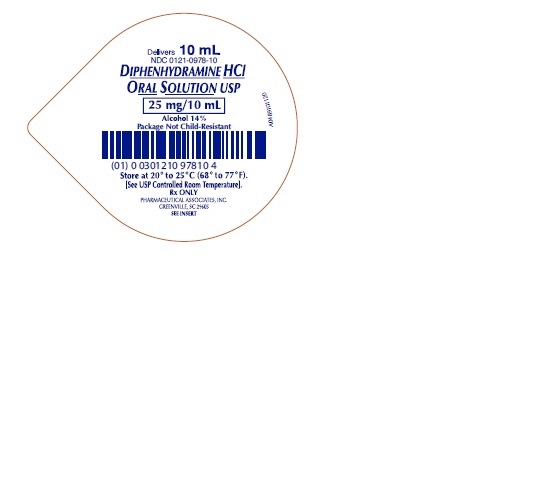 DRUG LABEL: DIPHENHYDRAMINE HYDROCHLORIDE
NDC: 0121-0489 | Form: SOLUTION
Manufacturer: PAI Holdings, LLC dba PAI Pharma
Category: prescription | Type: HUMAN PRESCRIPTION DRUG LABEL
Date: 20240405

ACTIVE INGREDIENTS: DIPHENHYDRAMINE HYDROCHLORIDE 12.5 mg/5 mL
INACTIVE INGREDIENTS: ALCOHOL; ANHYDROUS CITRIC ACID; D&C RED NO. 33; FD&C RED NO. 40; WATER; SODIUM CITRATE; SUCROSE

Diphenhydramine Hydrochloride Oral Solution USP

Rx ONLY

DESCRIPTION

Diphenhydramine hydrochloride is an antihistamine drug having the chemical name 2-(diphenylmethoxy)-N,N -dimethylethylamine hydrochloride and has the molecular formula C17H21NO•HCI (molecular weight 291.82). It occurs as a white odorless, crystalline powder and is freely soluble in water and alcohol. The structural formula is as follows:

Each 5 mL contains 12.5 mg of diphenhydramine hydrochloride and alcohol 14% for oral administration. Inactive Ingredients: Citric acid, D&C Red No. 33, FD&C Red No. 40, flavoring, purified water, sodium citrate, and sucrose.

CLINICAL PHARMACOLOGY

Diphenhydramine hydrochloride is an antihistamine with anticholinergic (drying) and sedative effects. Antihistamines appear to compete with histamine for cell receptor sites on effector cells.

A single oral dose of diphenhydramine hydrochloride is quickly absorbed with maximum activity occurring in approximately one hour. The duration of activity following an average dose of diphenhydramine hydrochloride is from four to six hours. Diphenhydramine is widely distributed throughout the body, including the CNS. Little, if any, is excreted unchanged in the urine; most appears as the degradation products of metabolic transformation in the liver, which are almost completely excreted within 24 hours.

INDICATIONS AND USAGE

Diphenhydramine hydrochloride in the oral form is effective for the following indications:

Antihistaminic

For allergic conjunctivitis due to foods; mild, uncomplicated allergic skin manifestations of urticaria and angioedema; amelioration of allergic reactions to blood or plasma; dermatographism; as therapy for anaphylactic reactions adjunctive to epinephrine and other standard measures after the acute manifestations have been controlled.

Motion Sickness

For active and prophylactic treatment of motion sickness.

Antiparkinsonism

For parkinsonism (including drug-induced) in the elderly unable to tolerate more potent agents; mild cases of parkinsonism (including drug-induced) in other age groups; in other cases of parkinsonism (including drug-induced) in combination with centrally acting anticholinergic agents.

Nighttime Sleep-aid.

CONTRAINDICATIONS

Use in Neonates or Premature Infants

This drug should not be used in neonates or premature infants.

Use in Nursing Mothers

Because of the higher risk of antihistamines for infants generally, and for neonates and prematures in particular, antihistamine therapy is contraindicated in nursing mothers.

Antihistamines are also contraindicated in the following conditions

Hypersensitivity to diphenhydramine hydrochloride and other antihistamines of similar chemical structure.

WARNINGS

Antihistamines should be used with considerable caution in patients with narrow-angle glaucoma, stenosing peptic ulcer, pyloroduodenal obstruction, symptomatic prostatic hypertrophy, or bladder-neck obstruction.

Use in Pediatric Patients

In pediatric patients, especially, antihistamines in overdosage may cause hallucinations, convulsions, or death. As in adults, antihistamines may diminish mental alertness in pediatric patients. In the young pediatric patient, particularly, they may produce excitation.

Use in the Elderly (approximately 60 years or older)

Antihistamines are most likely to cause dizziness, sedation, and hypotension in elderly patients.

PRECAUTIONS

General

Diphenhydramine hydrochloride has an atropine-like action and therefore, should be used with caution in patients with a history of bronchial asthma, increased intraocular pressure, hyperthyroidism, cardiovascular disease or hypertension. Use with caution in patients with lower respiratory disease including asthma.

Information for Patients

Patients taking diphenhydramine hydrochloride should be advised that this drug may cause drowsiness and has an additive effect with alcohol. Patients should be warned about engaging in activities requiring mental alertness such as driving a car or operating appliances, machinery, etc.

Drug Interactions

Diphenhydramine hydrochloride has additive effects with alcohol and other CNS depressants (hypnotics, sedatives, tranquilizers, etc.). MAO inhibitors prolong and intensify the anticholinergic (drying) effects of antihistamines.

Carcinogenesis, Mutagenesis, Impairment of Fertility

Long-term studies in animals to determine mutagenic and carcinogenic potential have not been performed.

Pregnancy

Pregnancy Category B

Reproduction studies have been performed in rats and rabbits at doses up to 5 times the human dose and have revealed no evidence of impaired fertility or harm to the fetus due to diphenhydramine hydrochloride. There are, however, no adequate and well-controlled studies in pregnant women. Because animal reproduction studies are not always predictive of human response, this drug should be used during pregnancy only if clearly needed.

Pediatric Use

Diphenhydramine hydrochloride should not be used in neonates and premature infants (see CONTRAINDICATIONS).

Diphenhydramine hydrochloride may diminish mental alertness, or, in the young pediatric patient, cause excitation. Overdosage may cause hallucinations, convulsions, or death (see WARNINGS and OVERDOSAGE).

See also DOSAGE AND ADMINISTRATION section.

ADVERSE REACTIONS

The most frequent adverse reactions are underscored.

- General: Urticaria, drug rash, anaphylactic shock, photosensitivity, excessive perspiration, chills, dryness of the mouth, nose and throat.
- Cardiovascular System: Hypotension, headache, palpitations, tachycardia, extrasystoles.
- Hematologic System: Hemolytic anemia, thrombocytopenia, agranulocytosis.
- Nervous System: Sedation, sleepiness, dizziness, disturbed coordination, fatigue, confusion, restlessness, excitation, nervousness, tremor, irritability, insomnia, euphoria, paresthesia, blurred vision, diplopia, vertigo, tinnitus, acute labyrinthitis, neuritis, convulsions.
- GI System: Epigastric distress, anorexia, nausea, vomiting, diarrhea, constipation.
- GU System: Urinary frequency, difficult urination, urinary retention, early menses.
- Respiratory System: Thickening of bronchial secretions, tightness of chest or throat and wheezing, nasal stuffiness.

To report SUSPECTED ADVERSE REACTIONS, contact Pharmaceutical Associates, Inc. at 1-800-845-8210 of FDA at 1-800-FDA-1088 or www.fda.gov/medwatch.

OVERDOSAGE

Antihistamine overdosage reactions may vary from central nervous system depression to stimulation. Stimulation is particularly likely in pediatric patients. Atropine-like signs and symptoms, dry mouth; fixed, dilated pupils; flushing and gastrointestinal symptoms may also occur.

If vomiting has not occurred spontaneously, the patient should be induced to vomit. This is best done by having him drink a glass of water or milk after which he should be made to gag. Precaution against aspiration must be taken, especially in infants and children.

If vomiting is unsuccessful, gastric lavage is indicated within 3 hours after ingestion and even later if large amounts of milk or cream were given beforehand. Isotonic or 1/2 isotonic saline is the lavage solution of choice.

Saline cathartics, as milk of magnesia, by osmosis draw water into the bowel and therefore are valuable for their action in rapid dilution of bowel content.

Stimulants should not be used.

Vasopressors may be used to treat hypotension.

DOSAGE AND ADMINISTRATION

DOSAGE SHOULD BE INDIVIDUALIZED ACCORDING TO THE NEEDS AND THE RESPONSE OF THE PATIENT.

A single oral dose of diphenhydramine hydrochloride is quickly absorbed with maximum activity occurring in approximately one hour. The duration of activity following an average dose of diphenhydramine hydrochloride is from four to six hours.

Adults

25 to 50 mg three to four times daily. The nightime sleep aid dosage is 50 mg at bedtime.

Pediatric Patients, other than premature infants and neonates

12.5 to 25 mg three or four times daily. Maximum daily dosage not to exceed 300 mg. For physicians who wish to calculate the dose on the basis of body weight or surface area, the recommended dosage is 5 mg/kg/24 hours or 150 mg/m2/24 hours.

Data are not available on the use of diphenhydramine hydrochloride as a nighttime sleep-aid in children under 12 years.

The basis for determining the most effective dosage regimen will be the response of the patient to medication and the condition under treatment.

In motion sickness, full dosage is recommended for prophylactic use, the first dose to be given 30 minutes before exposure to motion and similar doses before meals and upon retiring for the duration of exposure

STORAGE

Store at 20° to 25°C (68° to 77°F). [See USP Controlled Room Temperature]. Protect from freezing and light.

HOW SUPPLIED

Each 5 mL of Diphenhydramine Hydrochloride Oral Solution USP (clear purple/red liquid, cinnamon/anise flavor) contains 12.5 mg diphenhydramine hydrochloride with 14% alcohol and is supplied in the following oral dosage forms:

NDC 0121-0489-05: 5 mL unit dose cup

NDC 0121-0489-00: Case contains 100 unit dose cups of 5 mL (0121-0489-05) packaged in 10 trays of 10 unit dose cups each.

NDC 0121-0978-10: 10 mL unit dose cup

NDC 0121-0978-00: Case contains 100 unit dose cups of 10 mL (0121-0978-10) packaged in 10 trays of 10 unit dose cups each.

MANUFACTURED BY

Pharmaceutical
Associates, Inc.
Greenville, SC 29605
www.paipharma.com

R12/18

PRINCIPAL DISPLAY PANEL - 5 mL Unit Dose Cup Label

Delivers 5 mL
NDC 0121-0489-05

DIPHENHYDRAMINE HCl
ORAL SOLUTION USP
12.5 mg/5 mL

Alcohol 14%
Package Not Child-Resistant

Store at 20° to 25°C (68° to 77°F).
[See USP Controlled Room Temperature].
Rx ONLY

PHARMACEUTICAL ASSOCIATES, INC.
GREENVILLE, SC 29605

SEE INSERT

PRINCIPAL DISPLAY PANEL - 10 mL Unit Dose Cup Label

Delivers 10 mL
NDC 0121-0978-10

DIPHENHYDRAMINE HCl
ORAL SOLUTION USP

25 mg/10 mL

Alcohol 14%
Package Not Child-Resistant

Store at 20° to 25°C (68° to 77°F).
[See USP Controlled Room Temperature].
Rx ONLY

PHARMACEUTICAL ASSOCIATES, INC.
GREENVILLE, SC 29605

SEE INSERT